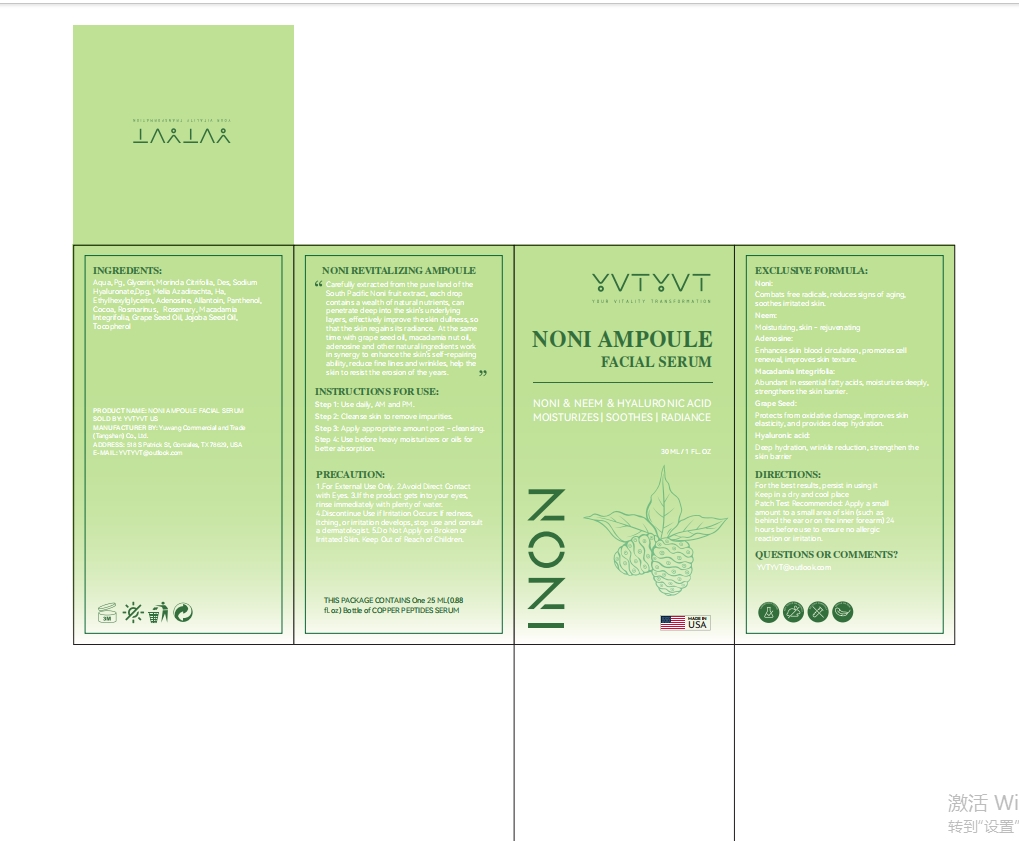 DRUG LABEL: YVTYVT NONI AMPOULE FACIAL SERUM
NDC: 85212-0019 | Form: LIQUID
Manufacturer: Beijing JUNGE Technology Co., Ltd.
Category: otc | Type: HUMAN OTC DRUG LABEL
Date: 20250228

ACTIVE INGREDIENTS: MORINDA CITRIFOLIA FRUIT 2 g/100 mL; ALLANTOIN 2 g/100 mL; MELIA AZADIRACHTA LEAF 1 g/100 mL; ADENOSINE 1 g/100 mL
INACTIVE INGREDIENTS: GLYCERIN 5 mL/100 mL; BUTYLENE GLYCOL 5 mL/100 mL; PROPYLENE GLYCOL 5 mL/100 mL; SUCROSE PALMITATE 0.1 mL/100 mL; COCOA 0.5 mL/100 mL; SIMMONDSIA CHINENSIS (JOJOBA) SEED OIL 0.1 mL/100 mL; DIPROPYLENE GLYCOL 1 mL/100 mL; DIETHOXYETHYL SUCCINATE 2 mL/100 mL; GLYCERYL POLYMETHACRYLATE (300000 MPA.S) 0.5 mL/100 mL; VITIS VINIFERA (GRAPE) SEED OIL 0.1 mL/100 mL; TOCOPHEROL 0.1 mL/100 mL; CETEARYL OLIVATE 0.5 mL/100 mL; SODIUM HYALURONATE 1 mL/100 mL; ETHYLHEXYLGLYCERIN 1 mL/100 mL; OCTYLDODECETH-16 1 mL/100 mL; 1,2-HEXANEDIOL 2 mL/100 mL; SODIUM POLYACRYLOYLDIMETHYL TAURATE 2 mL/100 mL; MAGNESIUM DISODIUM EDTA 0.5 mL/100 mL; SORBITAN OLIVATE 0.1 mL/100 mL; PANTHENOL 0.5 mL/100 mL; ROSMARINUS OFFICINALIS (ROSEMARY) LEAF OIL 0.5 mL/100 mL; MACADAMIA INTEGRIFOLIA SEED OIL 0.1 mL/100 mL; AQUA 65.4 mL/100 mL

DOSAGE AND ADMINISTRATION

Net Wt. 1FL. OZ (30 ml)

INSTRUCTIONS FOR USE

Step 1: Use daily, AM and PM.
Step 2: Cleanse skin to remove impurities.
Step 3: Apply appropriate amount post - cleansing.
Step 4: Use before heavy moisturizers or oils for better absorption.

PURPOSE

MOISTURIZES & SOOTHES & RADIANCE

Keep Out of Reach of Children.

WARNINGS

1.For External Use Only. 2.Avoid Direct Contact with Eyes. 3.If the product gets into your eyes, rinse immediately with plenty of water. 4.Discontinue Use if Irritation Occurs: If redness, itching, or irritation develops, stop use and consult a dermatologist. 5.Do Not Apply on Broken or Irritated Skin. Keep Out of Reach of Children.